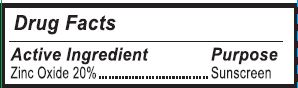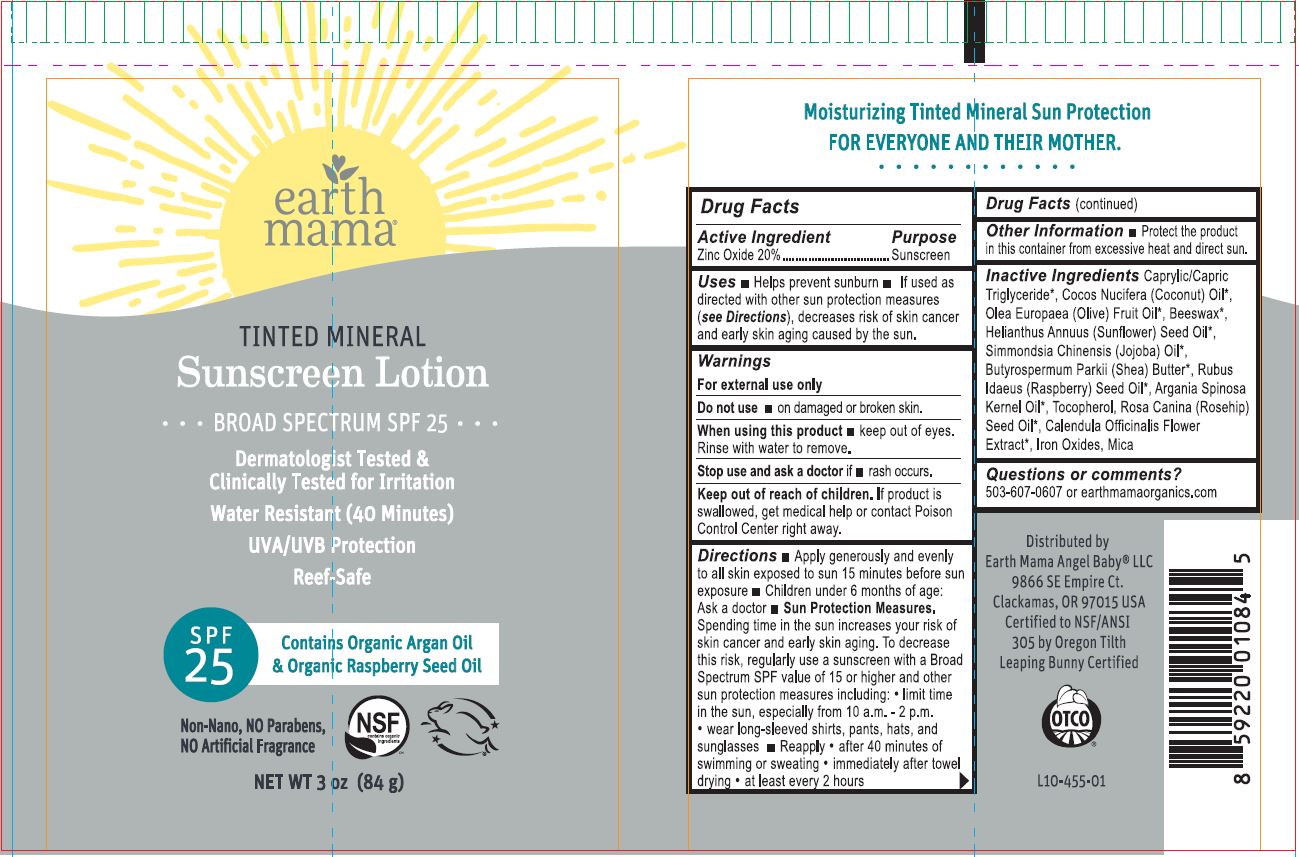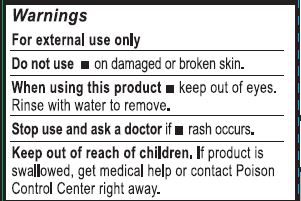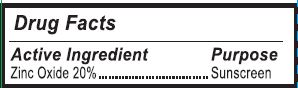 DRUG LABEL: Skin Protectant
NDC: 62932-228 | Form: LOTION
Manufacturer: Private Label Select Ltd CO
Category: otc | Type: HUMAN OTC DRUG LABEL
Date: 20220104

ACTIVE INGREDIENTS: ZINC OXIDE 20 g/100 g
INACTIVE INGREDIENTS: RASPBERRY SEED OIL; ARGAN OIL; WHITE WAX; SHEA BUTTER; .ALPHA.-TOCOPHEROL, D-; FERRIC OXIDE RED; MEDIUM-CHAIN TRIGLYCERIDES; SUNFLOWER OIL; OLIVE OIL; MICA; JOJOBA OIL; .GAMMA.-TOCOPHEROL; COCONUT OIL; .DELTA.-TOCOPHEROL; FERROSOFERRIC OXIDE; ROSA CANINA SEED; CALENDULA OFFICINALIS FLOWER; FERRIC OXYHYDROXIDE; .BETA.-TOCOPHEROL

Earth Mama Tinted Mineral Sunscreen Lotion Broad Spectrum SPF 25